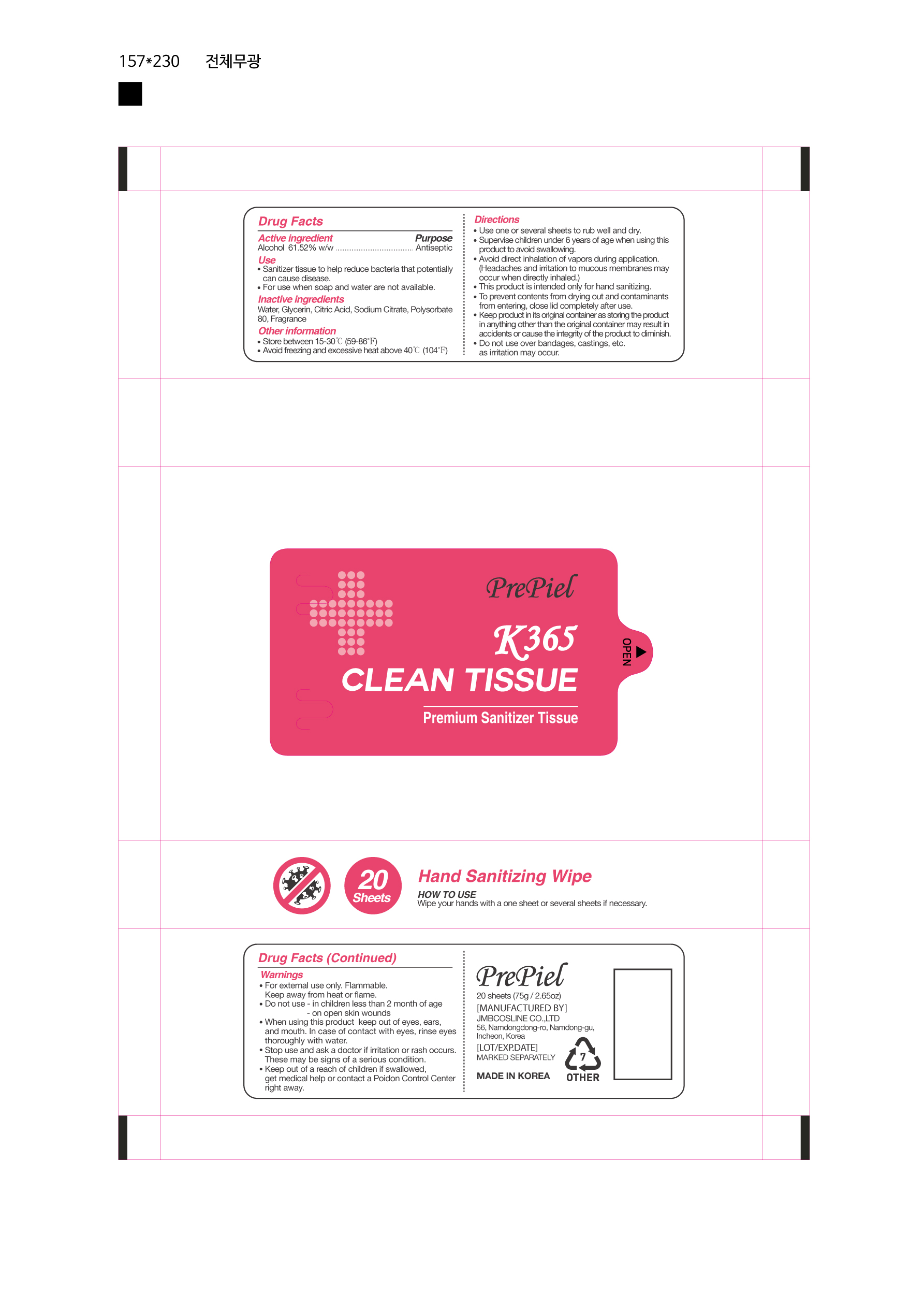 DRUG LABEL: Prepiel K365 CLEAN TISSUE
NDC: 90028-060 | Form: CLOTH
Manufacturer: JMB COSLINE CO.,LTD
Category: otc | Type: HUMAN OTC DRUG LABEL
Date: 20210209

ACTIVE INGREDIENTS: ALCOHOL 2.3 g/1 1
INACTIVE INGREDIENTS: WATER; GLYCERIN; POLYSORBATE 80; CITRIC ACID MONOHYDRATE; SODIUM CITRATE

JMB COSLINE CO.,LTD - Prepiel K365 CLEAN TISSUE
90028-060-01
20 SHEETS

Active ingredient

Alcohol 61.52% w/w .................................Antiseptic

Use

- Sanitizer tissue to help reduce bacteria that potentially can cause disease.
- For use when soap and water are not available.

Warnings

For external use only. Flammable. Keep away from heat or flame.

Do not use

■ in children less than 2 months of age ■ on open skin wounds

When using this product

keep out of eyes, ears, and mouth. In case of contact with eyes, rinse eyes thoroughly with water.

Stop use and ask a doctor

if irritation or rash occurs. These may be signs of a serious condition.

Keep out of reach of children

If swallowed, get medical help or contact a Poison Control Center right away.

Directions

■ Use one or several sheets to rub well and dry.

■ Supervise children under 6 years of age when using this product to avoid swallowing.
■ Avoid direct inhalation of vapors during application.

(Headaches and irritation to mucous membranes may occur when directly inhaled.)

■ This product is intended only for hand sanitizing.
■ To prevent contents from drying out and contaminants from entering, close
lid completely after use.
■ Keep product in its original container as storing the product in anything other than

the original container may result in accidents or cause the integrity of the product to diminish.
■ Do not use over bandages, castings, etc. as irritation may occur.

Other information

■ Store between 15-30 °C (59-86 °F)
■ Avoid freezing and excessive heat above 40 °C (104 °F)

Inactive ingredients

Water, Glycerin, Citric Acid, Sodium Citrate, Polysorbate 80, Fragrance